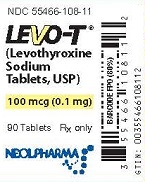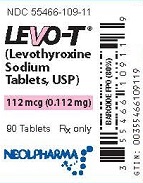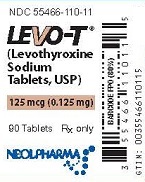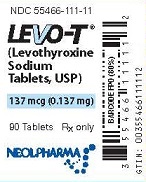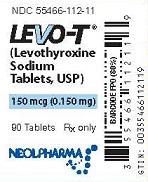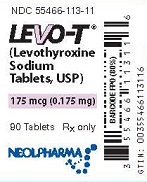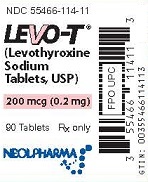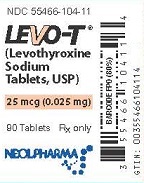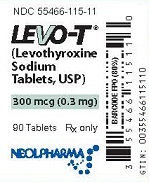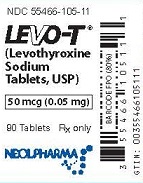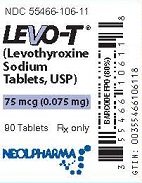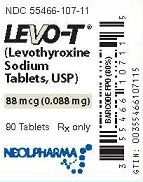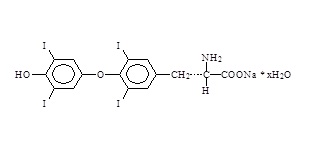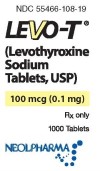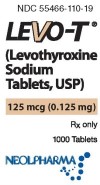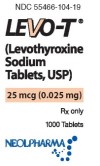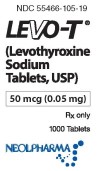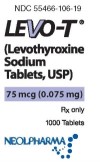 DRUG LABEL: LEVO-T
NDC: 55466-114 | Form: TABLET
Manufacturer: Neolpharma, Inc.
Category: prescription | Type: HUMAN PRESCRIPTION DRUG LABEL
Date: 20240418

ACTIVE INGREDIENTS: LEVOTHYROXINE SODIUM 200 ug/1 1
INACTIVE INGREDIENTS: D&C YELLOW NO. 10; D&C RED NO. 27 ALUMINUM LAKE; SILICON DIOXIDE; SODIUM STARCH GLYCOLATE TYPE A POTATO; MICROCRYSTALLINE CELLULOSE; MAGNESIUM STEARATE

HIGHLIGHTS OF PRESCRIBING INFORMATION

These highlights do not include all the information needed to use LEVO-T® safely and effectively. See full prescribing information for LEVO-T.
LEVO-T® (levothyroxine sodium) tablets, for oral use
Initial U.S. Approval:2002

WARNING: NOT FOR TREATMENT OF OBESITY OR FOR WEIGHT LOSS

See full prescribing information for complete boxed warning

- Thyroid hormones, including Levo-T should not be used for the treatment of obesity or for weight loss.
- Doses beyond the range of daily hormonal requirements may produce serious or even life threatening manifestations of toxicity (6, 10).

1 INDICATIONS AND USAGE

LEVO-T is L-thyroxine (T4) indicated for:

- Hypothyroidism: As replacement therapy in primary (thyroidal), secondary (pituitary), and tertiary (hypothalamic) congenital or acquired hypothyroidism. (1)
- Pituitary Thyrotropin (Thyroid-Stimulating Hormone, TSH) Suppression: As an adjunct to surgery and radioiodine therapy in the management of thyrotropin-dependent well-differentiated thyroid cancer. (1)
  Limitations of Use:

- Not indicated for suppression of benign thyroid nodules and nontoxic diffuse goiter in iodine-sufficient patients.

- Not indicated for treatment of hypothyroidism during the recovery phase of subacute thyroiditis.

2 DOSAGE AND ADMINISTRATION

- Administer once daily, preferably on an empty stomach, one-half to one hour before breakfast. (2.1)
- Administer at least 4 hours before or after drugs that are known to interfere with absorption. (2.1)
- Evaluate the need for dose adjustments when regularly administering within one hour of certain foods that may affect absorption. (2.1)
- Starting dose depends on a variety of factors, including age, body weight, cardiovascular status, and concomitant medications. Peak therapeutic effect may not be attained for 4-6 weeks. (2.2)
- See full prescribing information for dosing in specific patient populations. (2.3)
- Adequacy of therapy determined with periodic monitoring of TSH and/or T4 as well as clinical status. (2.4)

3 DOSAGE FORMS AND STRENGTHS

Tablets: 25, 50, 75, 88, 100, 112, 125, 137, 150, 175, 200, and 300 mcg (3)

4 CONTRAINDICATIONS

- Uncorrected adrenal insufficiency. (4)

5 WARNINGS AND PRECAUTIONS

- Cardiac adverse reactions in the elderly and in patients with underlying cardiovascular disease: Initiate LEVO-T at less than the full replacement dose because of the increased risk of cardiac adverse reactions, including atrial fibrillation. (2.3, 5.1, 8.5)
- Myxedema coma: Do not use oral thyroid hormone drug products to treat myxedema coma. (5.2)
- Acute adrenal crisis in patients with concomitant adrenal insufficiency: Treat with replacement glucocorticoids prior to initiation of LEVO-T treatment. (5.3)
- Prevention of hyperthyroidism or incomplete treatment of hypothyroidism: Proper dose titration and careful monitoring is critical to prevent the persistence of hypothyroidism or the development of hyperthyroidism. (5.4)
- Worsening of diabetic control: Therapy in patients with diabetes mellitus may worsen glycemic control and result in increased antidiabetic agent or insulin requirements. Carefully monitor glycemic control after starting, changing, or discontinuing thyroid hormone therapy. (5.5)
- Decreased bone mineral density associated with thyroid hormone over-replacement: Over-replacement can increase bone resorption and decrease bone mineral density. Give the lowest effective dose. (5.6)

6 ADVERSE REACTIONS

Adverse reactions associated with LEVO-T therapy are primarily those of hyperthyroidism due to therapeutic overdosage: arrhythmias, myocardial infarction, dyspnea, muscle spasm, headache, nervousness, irritability, insomnia, tremors, muscle weakness, increased appetite, weight loss, diarrhea, heat intolerance, menstrual irregularities, and skin rash. (6)

To report SUSPECTED ADVERSE REACTIONS, contact Neolpharma, Inc. at 1-844-200-4163 or FDA at 1-800-FDA-1088 or www.fda.gov/medwatch.

7 DRUG INTERACTIONS

See full prescribing information for drugs that affect thyroid hormone pharmacokinetics and metabolism (e.g., absorption, synthesis, secretion, catabolism, protein binding, and target tissue response) and may alter the therapeutic response to LEVO-T. (7)

8 USE IN SPECIFIC POPULATIONS

Pregnancy may require the use of higher doses of LEVO-T. (2.3, 8.1)

FULL PRESCRIBING INFORMATION

WARNING: NOT FOR TREATMENT OF OBESITY OR FOR WEIGHT LOSS

Thyroid hormones, including Levo-T, either alone or with other therapeutic agents, should not be used for the treatment of obesity or for weight loss.

In euthyroid patients, doses within the range of daily hormonal requirements are ineffective for weight reduction.

Larger doses may produce serious or even life threatening manifestations of toxicity, particularly when given in association with sympathomimetic amines such as those used for their anorectic effects [see Adverse Reactions (6), Drug Interactions (7.7), and Overdosage (10)] .

1 INDICATIONS AND USAGE

Hypothyroidism

LEVO-T is indicated as a replacement therapy in primary (thyroidal), secondary (pituitary), and tertiary (hypothalamic) congenital or acquired hypothyroidism.

Pituitary Thyrotropin (Thyroid-Stimulating Hormone, TSH) Suppression

LEVO-T is indicated as an adjunct to surgery and radioiodine therapy in the management of thyrotropin-dependent well-differentiated thyroid cancer.

Limitations of Use:

- LEVO-T is not indicated for suppression of benign thyroid nodules and nontoxic diffuse goiter in iodine-sufficient patients as there are no clinical benefits and overtreatment with LEVO-T may induce hyperthyroidism [see Warnings and Precautions (5.4)].
- LEVO-T is not indicated for treatment of hypothyroidism during the recovery phase of subacute thyroiditis.

2 DOSAGE AND ADMINISTRATION

2.1 General Administration Information

Take LEVO-T with a full glass of water as the tablet may rapidly disintegrate .

Administer LEVO-T as a single daily dose, on an empty stomach, one-half to one hour before breakfast.

Administer LEVO-T at least 4 hours before or after drugs known to interfere with LEVO-T absorption [see Drug Interactions (7.1)] .

Evaluate the need for dose adjustments when regularly administering within one hour of certain foods that may affect LEVO-T absorption [see Drug Interactions (7.9) and Clinical Pharmacology (12.3)] .

Administer LEVO-T to infants and children who cannot swallow intact tablets by crushing the tablet, suspending the freshly crushed tablet in a small amount (5 to 10 mL or 1 to 2 teaspoons) of water and immediately administering the suspension by spoon or dropper. Do not store the suspension. Do not administer in foods that decrease absorption of LEVO-T, such as soybean-based infant formula [see Drug Interactions (7.9)] .

2.2 General Principles of Dosing

The dose of LEVO-T for hypothyroidism or pituitary TSH suppression depends on a variety of factors including: the patient's age, body weight, cardiovascular status, concomitant medical conditions (including pregnancy), concomitant medications, co-administered food and the specific nature of the condition being treated [see Dosage and Administration (2.3), Warnings and Precautions (5), and Drug Interactions (7)] . Dosing must be individualized to account for these factors and dose adjustments made based on periodic assessment of the patient's clinical response and laboratory parameters [see Dosage and Administration (2.4)] .

The peak therapeutic effect of a given dose of LEVO-T may not be attained for 4 to 6 weeks.

2.3 Dosing in Specific Patient Populations

Primary Hypothyroidism in Adults and in Adolescents in Whom Growth and Puberty are Complete

Start LEVO-T at the full replacement dose in otherwise healthy, non-elderly individuals who have been hypothyroid for only a short time (such as a few months). The average full replacement dose of LEVO-T is approximately 1.6 mcg per kg per day (for example: 100 to 125 mcg per day for a 70 kg adult).

Adjust the dose by 12.5 to 25 mcg increments every 4 to 6 weeks until the patient is clinically euthyroid and the serum TSH returns to normal. Doses greater than 200 mcg per day are seldom required. An inadequate response to daily doses of greater than 300 mcg per day is rare and may indicate poor compliance, malabsorption, drug interactions, or a combination of these factors.

For elderly patients or patients with underlying cardiac disease, start with a dose of 12.5 to 25 mcg per day. Increase the dose every 6 to 8 weeks, as needed until the patient is clinically euthyroid and the serum TSH returns to normal. The full replacement dose of LEVO-T may be less than 1 mcg per kg per day in elderly patients.

In patients with severe longstanding hypothyroidism, start with a dose of 12.5 to 25 mcg per day. Adjust the dose in 12.5 to 25 mcg increments every 2 to 4 weeks until the patient is clinically euthyroid and the serum TSH level is normalized.

Secondary or Tertiary Hypothyroidism

Start LEVO-T at the full replacement dose in otherwise healthy, non-elderly individuals. Start with a lower dose in elderly patients, patients with underlying cardiovascular disease or patients with severe longstanding hypothyroidism as described above. Serum TSH is not a reliable measure of LEVO-T dose adequacy in patients with secondary or tertiary hypothyroidism and should not be used to monitor therapy. Use the serum free-T4 level to monitor adequacy of therapy in this patient population. Titrate LEVO-T dosing per above instructions until the patient is clinically euthyroid and the serum free-T4 level is restored to the upper half of the normal range.

Pediatric Dosage - Congenital or Acquired Hypothyroidism

The recommended daily dose of LEVO-T in pediatric patients with hypothyroidism is based on body weight and changes with age as described in Table 1. Start LEVO-T at the full daily dose in most pediatric patients. Start at a lower starting dose in newborns (0-3 months) at risk for cardiac failure and in children at risk for hyperactivity (see below). Monitor for clinical and laboratory response [see Dosage and Administration (2.4)].

Table 1. LEVO-T Dosing Guidelines for Pediatric Hypothyroidism
AGE | Daily Dose Per Kg Body Weight
0-3 months | 10-15 mcg/kg/day
3-6 months | 8-10 mcg/kg/day
6-12 months | 6-8 mcg/kg/day
1-5 years | 5-6 mcg/kg/day
6-12 years | 4-5 mcg/kg/day
Greater than 12 years but growth and puberty incomplete | 2-3 mcg/kg/day
Growth and puberty complete | 1.6 mcg/kg/day
a - The dose should be adjusted based on clinical response and laboratory parameters [see Dosage and Administration (2.4) and Use in Specific Populations (8.4)] .

Newborns (0-3 months) at risk for cardiac failure: Consider a lower starting dose in newborns at risk for cardiac failure. Increase the dose every 4 to 6 weeks as needed based on clinical and laboratory response.

Children at risk for hyperactivity: To minimize the risk of hyperactivity in children, start at one-fourth the recommended full replacement dose, and increase on a weekly basis by one-fourth the full recommended replacement dose until the full recommended replacement dose is reached.

Pregnancy

Pre-existing Hypothyroidism: LEVO-T dose requirements may increase during pregnancy. Measure serum TSH and free-T4 as soon as pregnancy is confirmed and, at minimum, during each trimester of pregnancy. In patients with primary hypothyroidism, maintain serum TSH in the trimester-specific reference range. For patients with serum TSH above the normal trimester-specific range, increase the dose of LEVO-T by 12.5 to 25 mcg/day and measure TSH every 4 weeks until a stable LEVO-T dose is reached and serum TSH is within the normal trimester-specific range. Reduce LEVO-T dosage to pre-pregnancy levels immediately after delivery and measure serum TSH levels 4 to 8 weeks postpartum to ensure LEVO-T dose is appropriate.

New Onset Hypothyroidism: Normalize thyroid function as rapidly as possible. In patients with moderate to severe signs and symptoms of hypothyroidism, start LEVO-T at the full replacement dose (1.6 mcg per kg body weight per day). In patients with mild hypothyroidism (TSH < 10 IU per liter) start LEVO-T at 1.0 mcg per kg body weight per day. Evaluate serum TSH every 4 weeks and adjust LEVO-T dosage until a serum TSH is within the normal trimester specific range [see Use in Specific Populations (8.1)] .

TSH Suppression in Well-differentiated Thyroid Cancer

Generally, TSH is suppressed to below 0.1 IU per liter, and this usually requires a LEVO-T dose of greater than 2 mcg per kg per day. However, in patients with high-risk tumors, the target level for TSH suppression may be lower.

2.4 Monitoring TSH and/or Thyroxine (T4) Levels

Assess the adequacy of therapy by periodic assessment of laboratory tests and clinical evaluation. Persistent clinical and laboratory evidence of hypothyroidism despite an apparent adequate replacement dose of LEVO-T may be evidence of inadequate absorption, poor compliance, drug interactions, or a combination of these factors.

Adults

In adult patients with primary hypothyroidism, monitor serum TSH levels after an interval of 6 to 8 weeks after any change in dose. In patients on a stable and appropriate replacement dose, evaluate clinical and biochemical response every 6 to 12 months and whenever there is a change in the patient's clinical status.

Pediatrics

In patients with congenital hypothyroidism, assess the adequacy of replacement therapy by measuring both serum TSH and total or free-T4. Monitor TSH and total or free-T4 in children as follows: 2 and 4 weeks after the initiation of treatment, 2 weeks after any change in dosage, and then every 3 to 12 months thereafter following dose stabilization until growth is completed. Poor compliance or abnormal values may necessitate more frequent monitoring. Perform routine clinical examination, including assessment of development, mental and physical growth, and bone maturation, at regular intervals.

While the general aim of therapy is to normalize the serum TSH level, TSH may not normalize in some patients due to in utero hypothyroidism causing a resetting of pituitary-thyroid feedback. Failure of the serum T4 to increase into the upper half of the normal range within 2 weeks of initiation of LEVO-T therapy and/or of the serum TSH to decrease below 20 IU per liter within 4 weeks may indicate the child is not receiving adequate therapy. Assess compliance, dose of medication administered, and method of administration prior to increasing the dose of LEVO-T [see Warnings and Precautions (5.1) and Use in Specific Populations (8.4)] .

Secondary and Tertiary Hypothyroidism

Monitor serum free-T4 levels and maintain in the upper half of the normal range in these patients.

3 DOSAGE FORMS AND STRENGTHS

LEVO-T tablets are available as follows:

Tablet Strength | Tablet Color/Shape | Tablet Markings
25 mcg | Orange/Caplet | "25" and "GG/331"
50 mcg | White/ Caplet | "50" and "GG/332"
75 mcg | Violet/ Caplet | "75" and "GG/333"
88 mcg | Olive Green/ Caplet | "88" and "GG/334"
100 mcg | Yellow/ Caplet | "100" and "GG/335"
112 mcg | Rose/ Caplet | "112" and "GG/336"
125 mcg | Brown/ Caplet | "125" and "GG/337"
137 mcg | Turquoise/ Caplet | "137" and "GG/330"
150 mcg | Blue/ Caplet | "150" and "GG/338"
175 mcg | Lilac/ Caplet | "175" and "GG/339"
200 mcg | Pink/ Caplet | "200" and "GG/340"
300 mcg | Green/ Caplet | "300" and "GG/341"

4 CONTRAINDICATIONS

LEVO-T is contraindicated in patients with uncorrected adrenal insufficiency [see Warnings and Precautions (5.3)] .

5 WARNINGS AND PRECAUTIONS

5.1 Cardiac Adverse Reactions in the Elderly and in Patients with Underlying Cardiovascular Disease

Over-treatment with levothyroxine may cause an increase in heart rate, cardiac wall thickness, and cardiac contractility and may precipitate angina or arrhythmias, particularly in patients with cardiovascular disease and in elderly patients. Initiate LEVO-T therapy in this population at lower doses than those recommended in younger individuals or in patients without cardiac disease [see Dosage and Administration (2.3), Use in Specific Populations (8.5)] .

Monitor for cardiac arrhythmias during surgical procedures in patients with coronary artery disease receiving suppressive LEVO-T therapy. Monitor patients receiving concomitant LEVO-T and sympathomimetic agents for signs and symptoms of coronary insufficiency.

If cardiac symptoms develop or worsen, reduce the LEVO-T dose or withhold for one week and restart at a lower dose.

5.2 Myxedema Coma

Myxedema coma is a life-threatening emergency characterized by poor circulation and hypometabolism, and may result in unpredictable absorption of levothyroxine sodium from the gastrointestinal tract. Use of oral thyroid hormone drug products is not recommended to treat myxedema coma. Administer thyroid hormone products formulated for intravenous administration to treat myxedema coma.

5.3 Acute Adrenal Crisis in Patients with Concomitant Adrenal Insufficiency

Thyroid hormone increases metabolic clearance of glucocorticoids. Initiation of thyroid hormone therapy prior to initiating glucocorticoid therapy may precipitate an acute adrenal crisis in patients with adrenal insufficiency. Treat patients with adrenal insufficiency with replacement glucocorticoids prior to initiating treatment with LEVO-T [see Contraindications (4)].

5.4 Prevention of Hyperthyroidism or Incomplete Treatment of Hypothyroidism

LEVO-T has a narrow therapeutic index. Over- or undertreatment with LEVO-T may have negative effects on growth and development, cardiovascular function, bone metabolism, reproductive function, cognitive function, emotional state, gastrointestinal function, and glucose and lipid metabolism. Titrate the dose of LEVO-T carefully and monitor response to titration to avoid these effects [see Dosage and Administration (2.4)] . Monitor for the presence of drug or food interactions when using LEVO-T and adjust the dose as necessary [see Drug Interactions (7.9) and Clinical Pharmacology (12.3)] .

5.5 Worsening of Diabetic Control

Addition of levothyroxine therapy in patients with diabetes mellitus may worsen glycemic control and result in increased antidiabetic agent or insulin requirements. Carefully monitor glycemic control after starting, changing, or discontinuing LEVO-T [see Drug Interactions (7.2)] .

5.6 Decreased Bone Mineral Density Associated with Thyroid Hormone Over-Replacement

Increased bone resorption and decreased bone mineral density may occur as a result of levothyroxine over-replacement, particularly in post-menopausal women. The increased bone resorption may be associated with increased serum levels and urinary excretion of calcium and phosphorous, elevations in bone alkaline phosphatase, and suppressed serum parathyroid hormone levels. Administer the minimum dose of LEVO-T that achieves the desired clinical and biochemical response to mitigate this risk.

6 ADVERSE REACTIONS

Adverse reactions associated with LEVO-T therapy are primarily those of hyperthyroidism due to therapeutic overdosage [see Warnings and Precautions (5), Overdosage (10)] . They include the following:

- General: fatigue, increased appetite, weight loss, heat intolerance, fever, excessive sweating
- Central nervous system: headache, hyperactivity, nervousness, anxiety, irritability, emotional lability, insomnia
- Musculoskeletal: tremors, muscle weakness, muscle spasm
- Cardiovascular: palpitations, tachycardia, arrhythmias, increased pulse and blood pressure, heart failure, angina, myocardial infarction, cardiac arrest
- Respiratory: dyspnea
- Gastrointestinal: diarrhea, vomiting, abdominal cramps, elevations in liver function tests
- Dermatologic: hair loss, flushing, rash
- Endocrine: decreased bone mineral density
- Reproductive: menstrual irregularities, impaired fertility

Seizures have been reported rarely with the institution of levothyroxine therapy.

Adverse Reactions in Children

Pseudotumor cerebri and slipped capital femoral epiphysis have been reported in children receiving levothyroxine therapy. Overtreatment may result in craniosynostosis in infants and premature closure of the epiphyses in children with resultant compromised adult height.

Hypersensitivity Reactions

Hypersensitivity reactions to inactive ingredients have occurred in patients treated with thyroid hormone products. These include urticaria, pruritus, skin rash, flushing, angioedema, various gastrointestinal symptoms (abdominal pain, nausea, vomiting and diarrhea), fever, arthralgia, serum sickness, and wheezing. Hypersensitivity to levothyroxine itself is not known to occur.

7 DRUG INTERACTIONS

7.1 Drugs Known to Affect Thyroid Hormone Pharmacokinetics

Many drugs can exert effects on thyroid hormone pharmacokinetics and metabolism (e.g., absorption, synthesis, secretion, catabolism, protein binding, and target tissue response) and may alter the therapeutic response to LEVO-T (see Tables 2-5 below).

Table 2. Drugs That May Decrease T4 Absorption (Hypothyroidism)
Potential impact: Concurrent use may reduce the efficacy of LEVO-T by binding and delaying or preventing absorption, potentially resulting in hypothyroidism.
Drug or Drug Class | Effect
Calcium Carbonate Ferrous Sulfate | Calcium carbonate may form an insoluble chelate with levothyroxine, and ferrous sulfate likely forms a ferric-thyroxine complex. Administer LEVO-T at least 4 hours apart from these agents.
Orlistat | Monitor patients treated concomitantly with orlistat and LEVO-T for changes in thyroid function.
Bile Acid Sequestrants -Colesevelam -Cholestyramine -Colestipol Ion Exchange Resins -Kayexalate -Sevelamer | Bile acid sequestrants and ion exchange resins are known to decrease levothyroxine absorption. Administer LEVO-T at least 4 hours prior to these drugs or monitor TSH levels.
Other drugs: Proton Pump Inhibitors Sucralfate Antacids - Aluminum & Magnesium Hydroxides - Simethicone | Gastric acidity is an essential requirement for adequate absorption of levothyroxine. Sucralfate, antacids and proton pump inhibitors may cause hypochlorhydria, affect intragastric pH, and reduce levothyroxine absorption. Monitor patients appropriately.

Table 3. Drugs That May Alter T4 and Triiodothyronine (T3) Serum Transport Without Affecting Free Thyroxine (FT4) Concentration (Euthyroidism)
Drug or Drug Class | Effect
Clofibrate Estrogen-containing oral contraceptives Estrogens (oral) Heroin / Methadone 5-Fluorouracil Mitotane Tamoxifen | These drugs may increase serum thyroxine-binding globulin (TBG) concentration.
Androgens / Anabolic Steroids Asparaginase Glucocorticoids Slow-Release Nicotinic Acid | These drugs may decrease serum TBG concentration.
Potential impact (below): Administration of these agents with LEVO-T results in an initial transient increase in FT4. Continued administration results in a decrease in serum T4 and normal FT4 and TSH concentrations.
Salicylates (> 2 g/day) | Salicylates inhibit binding of T4 and T3 to TBG and transthyretin. An initial increase in serum FT4 is followed by return of FT4 to normal levels with sustained therapeutic serum salicylate concentrations, although total T4 levels may decrease by as much as 30%.
Other drugs: Carbamazepine Furosemide (> 80 mg IV) Heparin Hydantoins Non-Steroidal Anti-inflammatory Drugs -Fenamates | These drugs may cause protein-binding site displacement. Furosemide has been shown to inhibit the protein binding of T4 to TBG and albumin, causing an increase free T4 fraction in serum. Furosemide competes for T4-binding sites on TBG, prealbumin, and albumin, so that a single high dose can acutely lower the total T4 level. Phenytoin and carbamazepine reduce serum protein binding of levothyroxine, and total and free T4 may be reduced by 20% to 40%, but most patients have normal serum TSH levels and are clinically euthyroid. Closely monitor thyroid hormone parameters.

Table 4. Drugs That May Alter Hepatic Metabolism of T4 (Hypothyroidism)
Potential impact: Stimulation of hepatic microsomal drug-metabolizing enzyme activity may cause increased hepatic degradation of levothyroxine, resulting in increased LEVO-T requirements.
Drug or Drug Class | Effect
Phenobarbital Rifampin | Phenobarbital has been shown to reduce the response to thyroxine. Phenobarbital increases L-thyroxine metabolism by inducing uridine 5'-diphospho-glucuronosyltransferase (UGT) and leads to a lower T4 serum levels. Changes in thyroid status may occur if barbiturates are added or withdrawn from patients being treated for hypothyroidism. Rifampin has been shown to accelerate the metabolism of levothyroxine.

Table 5. Drugs That May Decrease Conversion of T4 to T3
Potential impact: Administration of these enzyme inhibitors decreases the peripheral conversion of T4 to T3, leading to decreased T3 levels. However, serum T4 levels are usually normal but may occasionally be slightly increased.
Drug or Drug Class | Effect
Beta-adrenergic antagonists (e.g., Propranolol > 160 mg/day) | In patients treated with large doses of propranolol (> 160 mg/day), T3 and T4 levels change, TSH levels remain normal, and patients are clinically euthyroid. Actions of particular beta-adrenergic antagonists may be impaired when a hypothyroid patient is converted to the euthyroid state.
Glucocorticoids (e.g., Dexamethasone ≥ 4 mg/day) | Short-term administration of large doses of glucocorticoids may decrease serum T3 concentrations by 30% with minimal change in serum T4 levels. However, long-term glucocorticoid therapy may result in slightly decreased T3 and T4 levels due to decreased TBG production (See above).
Other drugs: Amiodarone | Amiodarone inhibits peripheral conversion of levothyroxine (T4) to triiodothyronine (T3) and may cause isolated biochemical changes (increase in serum free-T4, and decreased or normal free-T3) in clinically euthyroid patients.

7.2 Antidiabetic Therapy

Addition of LEVO-T therapy in patients with diabetes mellitus may worsen glycemic control and result in increased antidiabetic agent or insulin requirements. Carefully monitor glycemic control, especially when thyroid therapy is started, changed, or discontinued [see Warnings and Precautions (5.5)].

7.3 Oral Anticoagulants

LEVO-T increases the response to oral anticoagulant therapy. Therefore, a decrease in the dose of anticoagulant may be warranted with correction of the hypothyroid state or when the LEVO-T dose is increased. Closely monitor coagulation tests to permit appropriate and timely dosage adjustments.

7.4 Digitalis Glycosides

LEVO-T may reduce the therapeutic effects of digitalis glycosides. Serum digitalis glycoside levels may decrease when a hypothyroid patient becomes euthyroid, necessitating an increase in the dose of digitalis glycosides.

7.5 Antidepressant Therapy

Concurrent use of tricyclic (e.g., amitriptyline) or tetracyclic (e.g., maprotiline) antidepressants and LEVO-T may increase the therapeutic and toxic effects of both drugs, possibly due to increased receptor sensitivity to catecholamines. Toxic effects may include increased risk of cardiac arrhythmias and central nervous system stimulation. LEVO-T may accelerate the onset of action of tricyclics. Administration of sertraline in patients stabilized on LEVO-T may result in increased LEVO-T requirements.

7.6 Ketamine

Concurrent use of ketamine and LEVO-T may produce marked hypertension and tachycardia. Closely monitor blood pressure and heart rate in these patients.

7.7 Sympathomimetics

Concurrent use of sympathomimetics and LEVO-T may increase the effects of sympathomimetics or thyroid hormone. Thyroid hormones may increase the risk of coronary insufficiency when sympathomimetic agents are administered to patients with coronary artery disease.

7.8 Tyrosine-Kinase Inhibitors

Concurrent use of tyrosine-kinase inhibitors such as imatinib may cause hypothyroidism. Closely monitor TSH levels in such patients.

7.9 Drug-Food Interactions

Consumption of certain foods may affect LEVO-T absorption thereby necessitating adjustments in dosing [see Dosage and Administration (2.1)] . Soybean flour, cottonseed meal, walnuts, and dietary fiber may bind and decrease the absorption of LEVO-T from the gastrointestinal tract. Grapefruit juice may delay the absorption of levothyroxine and reduce its bioavailability.

7.10 Drug-Laboratory Test Interactions

Consider changes in TBG concentration when interpreting T4 and T3 values. Measure and evaluate unbound (free) hormone and/or determine the free-T4 index (FT4I) in this circumstance. Pregnancy, infectious hepatitis, estrogens, estrogen-containing oral contraceptives, and acute intermittent porphyria increase TBG concentration. Nephrosis, severe hypoproteinemia, severe liver disease, acromegaly, androgens, and corticosteroids decrease TBG concentration. Familial hyper- or hypo-thyroxine binding globulinemias have been described, with the incidence of TBG deficiency approximating 1 in 9000.

8 USE IN SPECIFIC POPULATIONS

8.1 Pregnancy

Risk Summary

Experience with levothyroxine use in pregnant women, including data from post-marketing studies, have not reported increased rates of major birth defects or miscarriages [see Data]. There are risks to the mother and fetus associated with untreated hypothyroidism in pregnancy. Since TSH levels may increase during pregnancy, TSH should be monitored and LEVO-T dosage adjusted during pregnancy [see Clinical Considerations] . There are no animal studies conducted with levothyroxine during pregnancy. LEVO-T should not be discontinued during pregnancy and hypothyroidism diagnosed during pregnancy should be promptly treated.

The estimated background risk of major birth defects and miscarriage for the indicated population is unknown. In the U.S. general population, the estimated background risk of major birth defects and miscarriage in clinically recognized pregnancies is 2 to 4% and 15 to 20%, respectively.

Clinical Considerations

Disease-Associated Maternal and/or Embryo/Fetal Risk

Maternal hypothyroidism during pregnancy is associated with a higher rate of complications, including spontaneous abortion, gestational hypertension, pre-eclampsia, stillbirth, and premature delivery. Untreated maternal hypothyroidism may have an adverse effect on fetal neurocognitive development.

Dose Adjustments During Pregnancy and the Postpartum Period

Pregnancy may increase LEVO-T requirements. Serum TSH levels should be monitored and the LEVO-T dosage adjusted during pregnancy. Since postpartum TSH levels are similar to preconception values, the LEVO-T dosage should return to the pre-pregnancy dose immediately after delivery [see Dosage and Administration (2.3)].

Data

Human Data

Levothyroxine is approved for use as a replacement therapy for hypothyroidism. There is a long experience of levothyroxine use in pregnant women, including data from post-marketing studies that have not reported increased rates of fetal malformations, miscarriages or other adverse maternal or fetal outcomes associated with levothyroxine use in pregnant women.

8.2 Lactation

Risk Summary

Limited published studies report that levothyroxine is present in human milk. However, there is insufficient information to determine the effects of Levothyroxine on the breastfed infant and no available information on the effects of levothyroxine on milk production. Adequate levothyroxine treatment during lactation may normalize milk production in hypothyroid lactating mothers. The developmental and health benefits of breastfeeding should be considered along with the mother's clinical need for LEVO-T and any potential adverse effects on the breastfed infant from LEVO-T or from the underlying maternal condition.

8.4 Pediatric Use

The initial dose of LEVO-T varies with age and body weight. Dosing adjustments are based on an assessment of the individual patient's clinical and laboratory parameters [see Dosage and Administration (2.3, 2.4)] .

In children in whom a diagnosis of permanent hypothyroidism has not been established, discontinue LEVO-T administration for a trial period, but only after the child is at least 3 years of age. Obtain serum T4 and TSH levels at the end of the trial period, and use laboratory test results and clinical assessment to guide diagnosis and treatment, if warranted.

Congenital Hypothyroidism [See Dosage and Administration (2.3, 2.4)]

Rapid restoration of normal serum T4 concentrations is essential for preventing the adverse effects of congenital hypothyroidism on intellectual development as well as on overall physical growth and maturation. Therefore, initiate LEVO-T therapy immediately upon diagnosis. Levothyroxine is generally continued for life in these patients.

Closely monitor infants during the first 2 weeks of LEVO-T therapy for cardiac overload, arrhythmias, and aspiration from avid suckling.

Closely monitor patients to avoid undertreatment or overtreatment. Undertreatment may have deleterious effects on intellectual development and linear growth. Overtreatment is associated with craniosynostosis in infants, may adversely affect the tempo of brain maturation, and may accelerate the bone age and result in premature epiphyseal closure and compromised adult stature.

Acquired Hypothyroidism in Pediatric Patients

Closely monitor patients to avoid undertreatment and overtreatment. Undertreatment may result in poor school performance due to impaired concentration and slowed mentation and in reduced adult height. Overtreatment may accelerate the bone age and result in premature epiphyseal closure and compromised adult stature.

Treated children may manifest a period of catch-up growth, which may be adequate in some cases to normalize adult height. In children with severe or prolonged hypothyroidism, catch-up growth may not be adequate to normalize adult height.

8.5 Geriatric Use

Because of the increased prevalence of cardiovascular disease among the elderly, initiate LEVO-T at less than the full replacement dose [see Warnings and Precautions (5.1) and Dosage and Administration (2.3)] . Atrial arrhythmias can occur in elderly patients. Atrial fibrillation is the most common of the arrhythmias observed with levothyroxine overtreatment in the elderly.

10 OVERDOSAGE

The signs and symptoms of overdosage are those of hyperthyroidism [see Warnings and Precautions (5) and Adverse Reactions (6)] . In addition, confusion and disorientation may occur. Cerebral embolism, shock, coma, and death have been reported. Seizures occurred in a 3-year-old child ingesting 3.6 mg of levothyroxine. Symptoms may not necessarily be evident or may not appear until several days after ingestion of levothyroxine sodium.

Reduce the LEVO-T dose or discontinue temporarily if signs or symptoms of overdosage occur. Initiate appropriate supportive treatment as dictated by the patient's medical status.

For current information on the management of poisoning or overdosage, contact the National Poison Control Center at 1-800-222-1222 or www.poison.org.

11 DESCRIPTION

LEVO-T (levothyroxine sodium tablets, USP) contain synthetic crystalline L-3,3',5,5'-tetraiodothyronine sodium salt [levothyroxine (T4) sodium]. Synthetic T4 is chemically identical to that produced in the human thyroid gland. Levothyroxine (T4) sodium has an empirical formula of C15H10I4NNaO4∙xH2O (where x = 5), molecular weight of 798.86 g/mol (anhydrous), and structural formula as shown:

LEVO-T tablets for oral administration are supplied in the following strengths: 25 mcg, 50 mcg, 75 mcg, 88 mcg, 100 mcg, 112 mcg, 125 mcg, 137 mcg, 150 mcg, 175 mcg, 200 mcg, and 300 mcg. Each LEVO-T tablet contains the inactive ingredients Magnesium Stearate, NF; Microcrystalline Cellulose, NF; Colloidal Silicone Dioxide, NF; and Sodium Starch Glycolate, NF. Each tablet strength meets USP Dissolution Test 2. Table 6 provides a listing of the color additives by tablet strength:

Table 6. LEVO-T Tablets Color Additives
Strength (mcg) | Color additive(s)
25 | FD&C Yellow No. 6 Aluminum Lake
50 | None
75 | FD&C Blue No. 2 Aluminum Lake, D&C Red No. 27 Aluminum Lake
88 | FD&C Blue No. 1 Aluminum Lake, D&C Yellow No. 10 Aluminum Lake, D&C Red No. 30 Aluminum Lake
100 | D&C Yellow No. 10 Aluminum Lake, D&C Red Lake Blend (D&C Red No. 27 Lake and D&C Red No. 30 Lake)
112 | D&C Red No. 27 Aluminum Lake, D&C Red No. 30 Aluminum Lake
125 | FD&C Yellow No. 6 Aluminum Lake, FD&C Red No. 40 Aluminum Lake, FD&C Blue No. 1 Aluminum Lake
137 | FD&C Blue No. 1 Aluminum Lake
150 | FD&C Blue No. 2 Aluminum Lake
175 | D&C Red No. 27 Aluminum Lake, D&C Red No. 30 Aluminum Lake, FD&C Blue No. 1 Aluminum Lake
200 | D&C Yellow No. 10 Aluminum Lake, D&C Red No. 27 Aluminum Lake
300 | D&C Yellow No. 10 Aluminum Lake, FD&C Yellow No. 6 Aluminum Lake, FD&C Blue No. 1 Aluminum Lake

12 CLINICAL PHARMACOLOGY

12.1 Mechanism of Action

Thyroid hormones exert their physiologic actions through control of DNA transcription and protein synthesis. Triiodothyronine (T3) and L-thyroxine (T4) diffuse into the cell nucleus and bind to thyroid receptor proteins attached to DNA. This hormone nuclear receptor complex activates gene transcription and synthesis of messenger RNA and cytoplasmic proteins.

The physiological actions of thyroid hormones are produced predominantly by T3, the majority of which (approximately 80%) is derived from T4 by deiodination in peripheral tissues.

12.2 Pharmacodynamics

Oral levothyroxine sodium is a synthetic T4 hormone that exerts the same physiologic effect as endogenous T4, thereby maintaining normal T4 levels when a deficiency is present.

12.3 Pharmacokinetics

Absorption

Absorption of orally administered T4 from the gastrointestinal tract ranges from 40% to 80%. The majority of the LEVO-T dose is absorbed from the jejunum and upper ileum. The relative bioavailability of LEVO-T tablets, compared to an equal nominal dose of oral levothyroxine sodium solution, is approximately 99%. T4 absorption is increased by fasting, and decreased in malabsorption syndromes and by certain foods such as soybeans. Dietary fiber decreases bioavailability of T4. Absorption may also decrease with age. In addition, many drugs and foods affect T4 absorption [see Drug Interactions (7)] .

Distribution

Circulating thyroid hormones are greater than 99% bound to plasma proteins, including thyroxine-binding globulin (TBG), thyroxine-binding prealbumin (TBPA), and albumin (TBA), whose capacities and affinities vary for each hormone. The higher affinity of both TBG and TBPA for T4 partially explains the higher serum levels, slower metabolic clearance, and longer half-life of T4 compared to T3. Protein-bound thyroid hormones exist in reverse equilibrium with small amounts of free hormone. Only unbound hormone is metabolically active. Many drugs and physiologic conditions affect the binding of thyroid hormones to serum proteins [see Drug Interactions (7)] . Thyroid hormones do not readily cross the placental barrier [see Use in Specific Populations (8.1)] .

Elimination

Metabolism

T4 is slowly eliminated (see Table 7). The major pathway of thyroid hormone metabolism is through sequential deiodination. Approximately 80% of circulating T3 is derived from peripheral T4 by monodeiodination. The liver is the major site of degradation for both T4 and T3, with T4 deiodination also occurring at a number of additional sites, including the kidney and other tissues. Approximately 80% of the daily dose of T4 is deiodinated to yield equal amounts of T3 and reverse T3 (rT3). T3 and rT3 are further deiodinated to diiodothyronine. Thyroid hormones are also metabolized via conjugation with glucuronides and sulfates and excreted directly into the bile and gut where they undergo enterohepatic recirculation.

Excretion

Thyroid hormones are primarily eliminated by the kidneys. A portion of the conjugated hormone reaches the colon unchanged and is eliminated in the feces. Approximately 20% of T4 is eliminated in the stool. Urinary excretion of T4 decreases with age.

Table 7. Pharmacokinetic Parameters of Thyroid Hormones in Euthyroid Patients
Hormone | Ratio in Thyroglobulin | Biologic Potency | t1/2 (days) | Protein Binding (%)
Levothyroxine (T4) | 10 - 20 | 1 | 6-7b | 99.96
Liothyronine (T3) | 1 | 4 | ≤ 2 | 99.5
a - Includes TBG, TBPA, and TBA
b - 3 to 4 days in hyperthyroidism, 9 to 10 days in hypothyroidism

13 NONCLINICAL TOXICOLOGY

13.1 Carcinogenesis, Mutagenesis, Impairment of Fertility

Standard animal studies have not been performed to evaluate the carcinogenic potential, mutagenic potential or effects on fertility of levothyroxine.

16 HOW SUPPLIED/STORAGE AND HANDLING

LEVO-T (levothyroxine sodium, USP) tablets are supplied as follows:

Strength (mcg) | Color/Shape | Tablet Markings | NDC# for bottles of 90 | NDC # for bottles of 1000
25 | Orange/Caplet | "25" and "GG/331" | 55466-104-11 | 55466-104-19
50 | White/ Caplet | "50" and "GG/332" | 55466-105-11 | 55466-105-19
75 | Violet/ Caplet | "75" and "GG/333" | 55466-106-11 | 55466-106-19
88 | Olive Green/ Caplet | "88" and 'GG/334" | 55466-107-11 | --
100 | Yellow/ Caplet | "100" and "GG/335" | 55466-108-11 | 55466-108-19
112 | Rose/ Caplet | "112" and "GG/336" | 55466-109-11 | --
125 | Brown/ Caplet | "125" and "GG/337" | 55466-110-11 | 55466-110-19
137 | Turquoise/ Caplet | "137" and "GG/330" | 55466-111-11 | --
150 | Blue/ Caplet | "150" and "GG/338" | 55466-112-11 | --
175 | Lilac/ Caplet | "175" and "GG/339" | 55466-113-11 | --
200 | Pink/ Caplet | "200" and "GG/340" | 55466-114-11 | --
300 | Green/ Caplet | "300" and "GG/341" | 55466-115-11 | --

Storage Conditions

Store at 25°C (77°F); excursions permitted to 15° to 30° C (59° to 86° F) [see USP Controlled Room Temperature]. LEVO-T tablets should be protected from light and moisture.

17 PATIENT COUNSELING INFORMATION

Inform the patient of the following information to aid in the safe and effective use of LEVO-T:

Dosing and Administration

- Instruct patients that LEVO-T should be taken with a full glass of water since the tablet may rapidly disintegrate.
- Instruct patients to take LEVO-T only as directed by their healthcare provider.
- Instruct patients to take LEVO-T as a single dose, preferably on an empty stomach, one-half to one hour before breakfast.
- Inform patients that agents such as iron and calcium supplements and antacids can decrease the absorption of levothyroxine. Instruct patients not to take LEVO-T tablets within 4 hours of these agents.
- Instruct patients to notify their healthcare provider if they are pregnant or breastfeeding or are thinking of becoming pregnant while taking LEVO-T.

Important Information

- Inform patients that it may take several weeks before they notice an improvement in symptoms.
- Inform patients that the levothyroxine in LEVO-T is intended to replace a hormone that is normally produced by the thyroid gland. Generally, replacement therapy is to be taken for life.
- Inform patients that LEVO-T should not be used as a primary or adjunctive therapy in a weight control program.
- Instruct patients to notify their healthcare provider if they are taking any other medications, including prescription and over-the-counter preparations.
- Instruct patients to notify their physician of any other medical conditions they may have, particularly heart disease, diabetes, clotting disorders, and adrenal or pituitary gland problems, as the dose of medications used to control these other conditions may need to be adjusted while they are taking LEVO-T. If they have diabetes, instruct patients to monitor their blood and/or urinary glucose levels as directed by their physician and immediately report any changes to their physician. If patients are taking anticoagulants, their clotting status should be checked frequently.
- Instruct patients to notify their physician or dentist that they are taking LEVO-T prior to any surgery.

Adverse Reactions

- Instruct patients to notify their healthcare provider if they experience any of the following symptoms: rapid or irregular heartbeat, chest pain, shortness of breath, leg cramps, headache, nervousness, irritability, sleeplessness, tremors, change in appetite, weight gain or loss, vomiting, diarrhea, excessive sweating, heat intolerance, fever, changes in menstrual periods, hives or skin rash, or any other unusual medical event.
- Inform patients that partial hair loss may occur rarely during the first few months of LEVO-T therapy, but this is usually temporary.